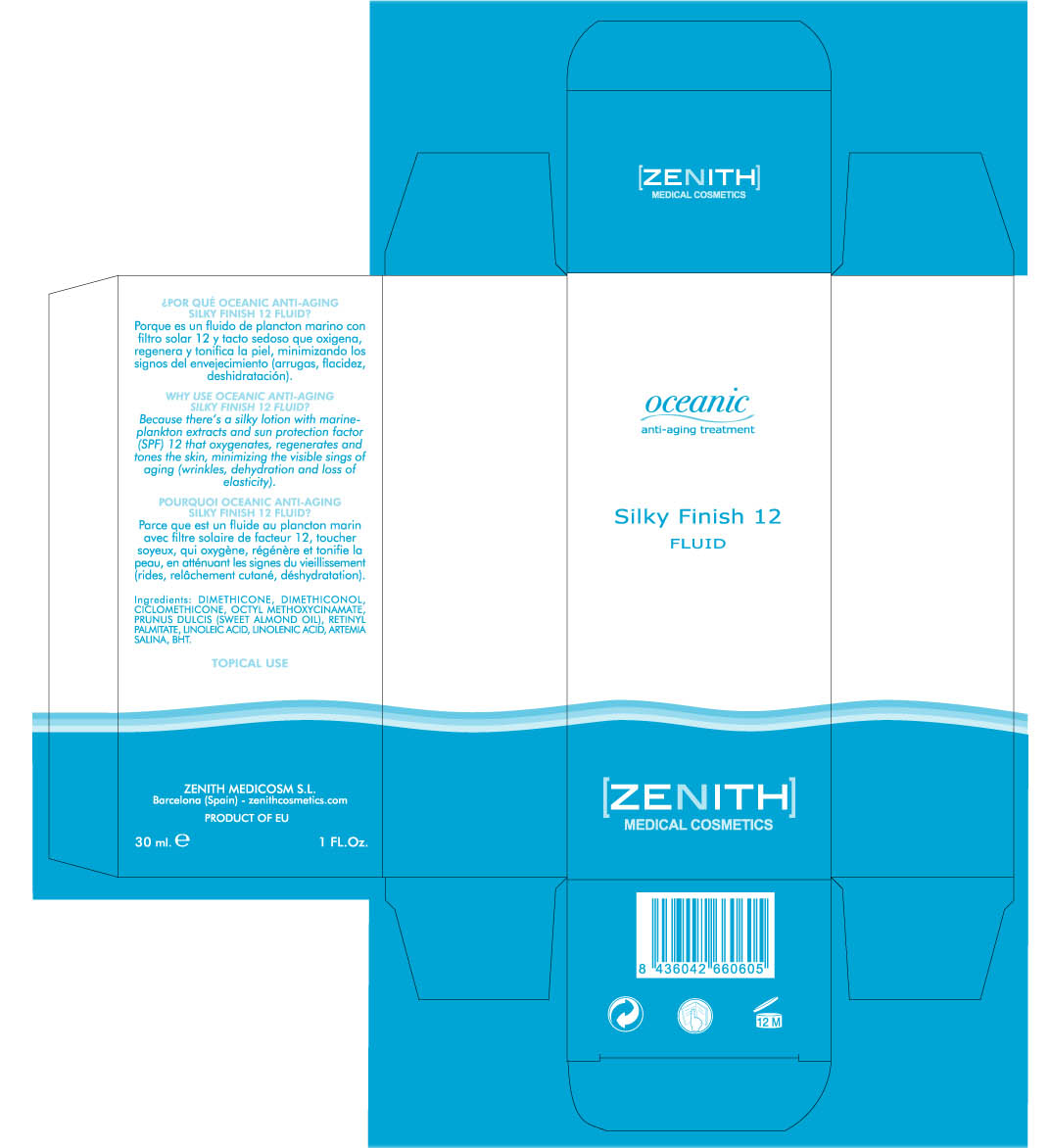 DRUG LABEL: Silky Finish
NDC: 42248-128 | Form: LOTION
Manufacturer: Zenith Medicosm SL
Category: otc | Type: HUMAN OTC DRUG LABEL
Date: 20120220

ACTIVE INGREDIENTS: OCTINOXATE 2.25 mL/30 mL
INACTIVE INGREDIENTS: DIMETHICONE; DIMETHICONOL (41 MPA.S); CYCLOMETHICONE; ALMOND OIL; VITAMIN A PALMITATE; LINOLEIC ACID; LINOLENIC ACID; BUTYLATED HYDROXYTOLUENE

Drug Facts

Active Ingredient

Octinoxate 7.5%

Description

WHY USE OCEANIC ANTI-AGING SILKY FINISH FLUID

Because there's a silky lotion with marine-plankton extracts and sun protection (SPF) 12 that oxygenates, regenerates and tones the skin, minimizing the visible signs of aging (wrinkles, dehydration and loss of elasticity).

30ml. 1 FL.oz

Warning

TOPICAL USE